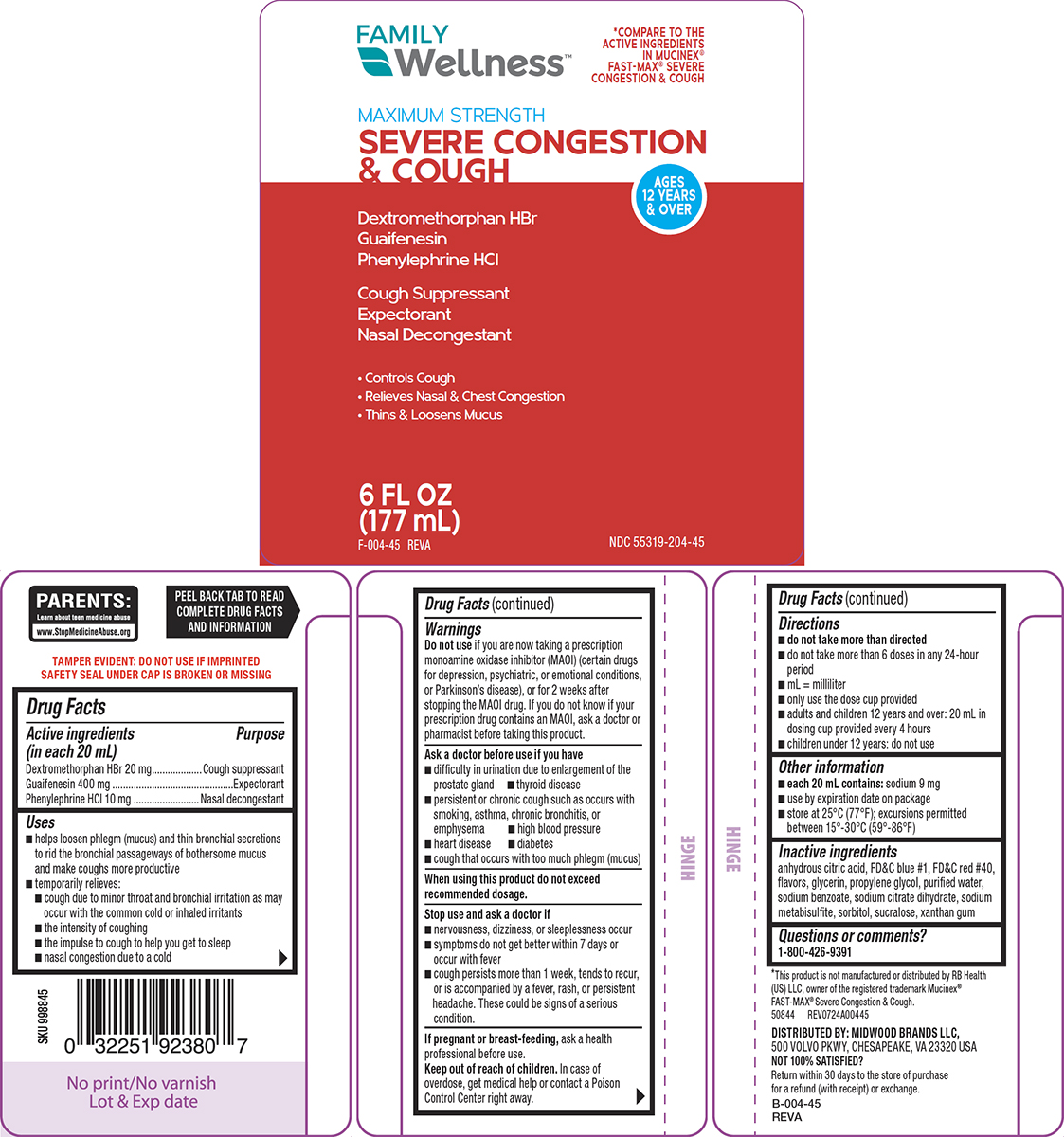 DRUG LABEL: Severe Congestion and Cough
NDC: 55319-204 | Form: SOLUTION
Manufacturer: Family Dollar Services Inc
Category: otc | Type: HUMAN OTC DRUG LABEL
Date: 20260106

ACTIVE INGREDIENTS: DEXTROMETHORPHAN HYDROBROMIDE 20 mg/20 mL; GUAIFENESIN 400 mg/20 mL; PHENYLEPHRINE HYDROCHLORIDE 10 mg/20 mL
INACTIVE INGREDIENTS: ANHYDROUS CITRIC ACID; FD&C BLUE NO. 1; FD&C RED NO. 40; GLYCERIN; PROPYLENE GLYCOL; WATER; SODIUM BENZOATE; TRISODIUM CITRATE DIHYDRATE; SODIUM METABISULFITE; SORBITOL; SUCRALOSE; XANTHAN GUM

Family Wellness 44-004

Active ingredients (in each 20 mL)

Dextromethorphan HBr 20 mg
Guaifenesin 400 mg
Phenylephrine HCl 10 mg

Purpose

Cough suppressant
Expectorant
Nasal decongestant

Uses

- helps loosen phlegm (mucus) and thin bronchial secretions to rid the bronchial passageways of bothersome mucus and make coughs more productive
- temporarily relieves:
  - cough due to minor throat and bronchial irritation as may occur with the common cold or inhaled irritants
  - the intensity of coughing
  - the impulse to cough to help you get to sleep
  - nasal congestion due to a cold

Warnings

Do not use

if you are now taking a prescription monoamine oxidase inhibitor (MAOI) (certain drugs for depression, psychiatric, or emotional conditions, or Parkinson’s disease), or for 2 weeks after stopping the MAOI drug. If you do not know if your prescription drug contains an MAOI, ask a doctor or pharmacist before taking this product.

Ask a doctor before use if you have

- difficulty in urination due to enlargement of the prostate gland
- thyroid disease
- persistent or chronic cough such as occurs with smoking, asthma, chronic bronchitis, or emphysema
- high blood pressure
- heart disease
- diabetes
- cough that occurs with too much phlegm (mucus)

When using this product

do not exceed recommended dosage.

Stop use and ask a doctor if

- nervousness, dizziness, or sleeplessness occur
- symptoms do not get better within 7 days or occur with fever
- cough persists more than 1 week, tends to recur, or is accompanied by a fever, rash, or persistent headache. These could be signs of a serious condition.

If pregnant or breast-feeding,

ask a health professional before use.

Keep out of reach of children.

In case of overdose, get medical help or contact a Poison Control Center right away.

Directions

- do not take more than directed
- do not take more than 6 doses in any 24-hour period
- mL = milliliter
- only use the dose cup provided
- adults and children 12 years and over: 20 mL in dosing cup provided every 4 hours
- children under 12 years: do not use

Other information

- each 20 mL contains: sodium 9 mg
- use by expiration date on package
- store at 25°C (77°F); excursions permitted between 15°-30°C (59°-86°F)

Inactive ingredients

anhydrous citric acid, FD&C blue #1, FD&C red #40, flavors, glycerin, propylene glycol, purified water, sodium benzoate, sodium citrate dihydrate, sodium metabisulfite, sorbitol, sucralose, xanthan gum

Questions or comments?

1-800-426-9391

Principal Display Panel

FAMILY
Wellness™

*COMPARE TO THE
ACTIVE INGREDIENTS
IN MUCINEX®
FAST-MAX® SEVERE
CONGESTION & COUGH

MAXIMUM STRENGTH
SEVERE CONGESTION
& COUGH

Dextromethorphan HBr
Guaifenesin
Phenylephrine HCl

Cough Suppressant
Expectorant
Nasal Decongestant

• Controls Cough
• Relieves Nasal & Chest Congestion
• Thins & Loosens Mucus

AGES
12 YEARS
& OVER

6 FL OZ
(177 mL)

NDC 55319-204-45

TAMPER EVIDENT: DO NOT USE IF IMPRINTED
SAFETY SEAL UNDER CAP IS BROKEN OR MISSING

PARENTS:
Learn about teen medicine abuse
www.StopMedicineAbuse.org

*This product is not manufactured or distributed by RB Health
(US) LLC, owner of the registered trademark Mucinex®
FAST-MAX® Severe Congestion & Cough.
50844 REV0724A00445

DISTRIBUTED BY: MIDWOOD BRANDS LLC,
500 VOLVO PKWY, CHESAPEAKE, VA 23320 USA
NOT 100% SATISFIED?
Return within 30 days to the store of purchase
for a refund (with receipt) or exchange.

Family Wellness 44-004